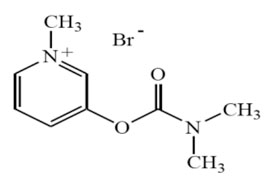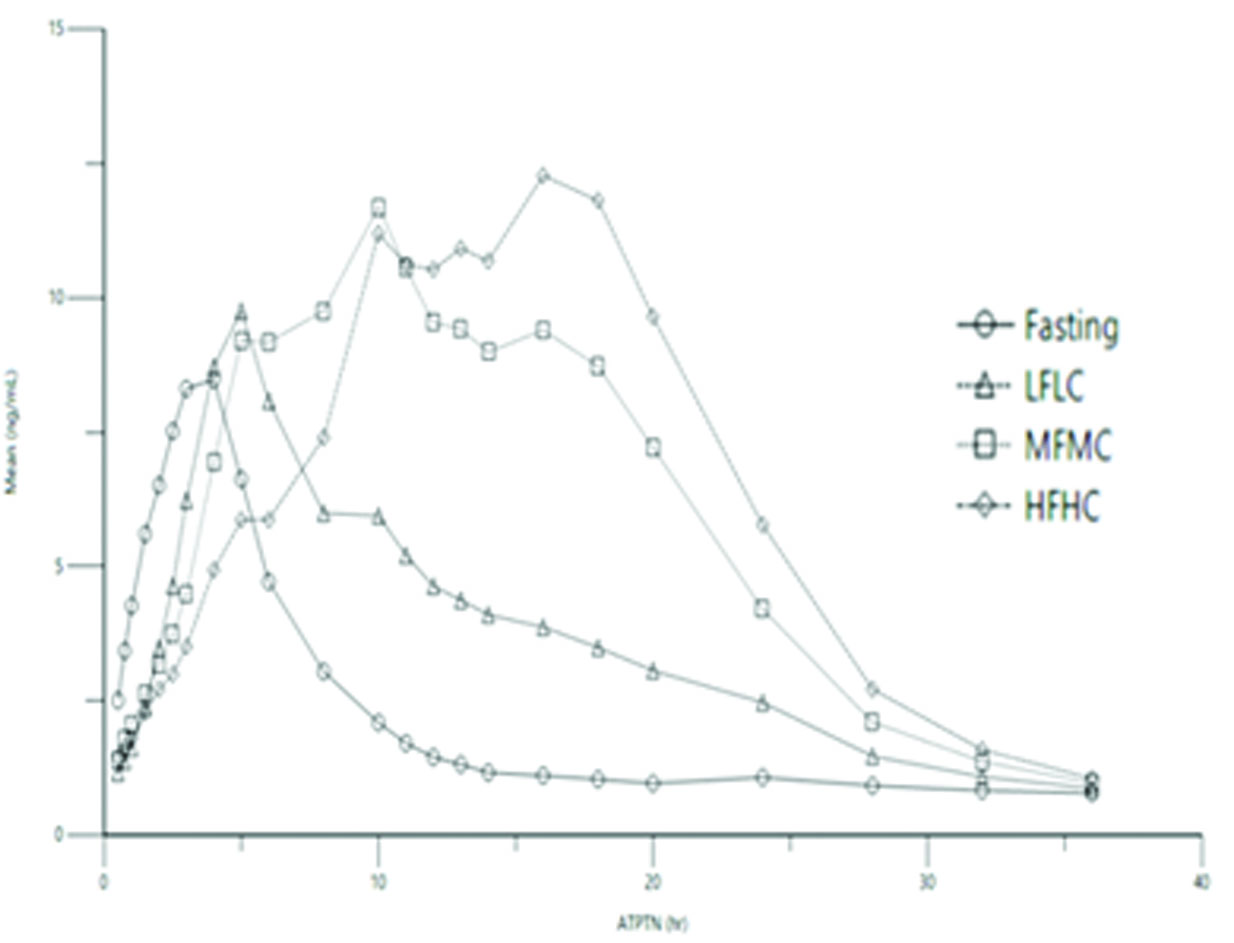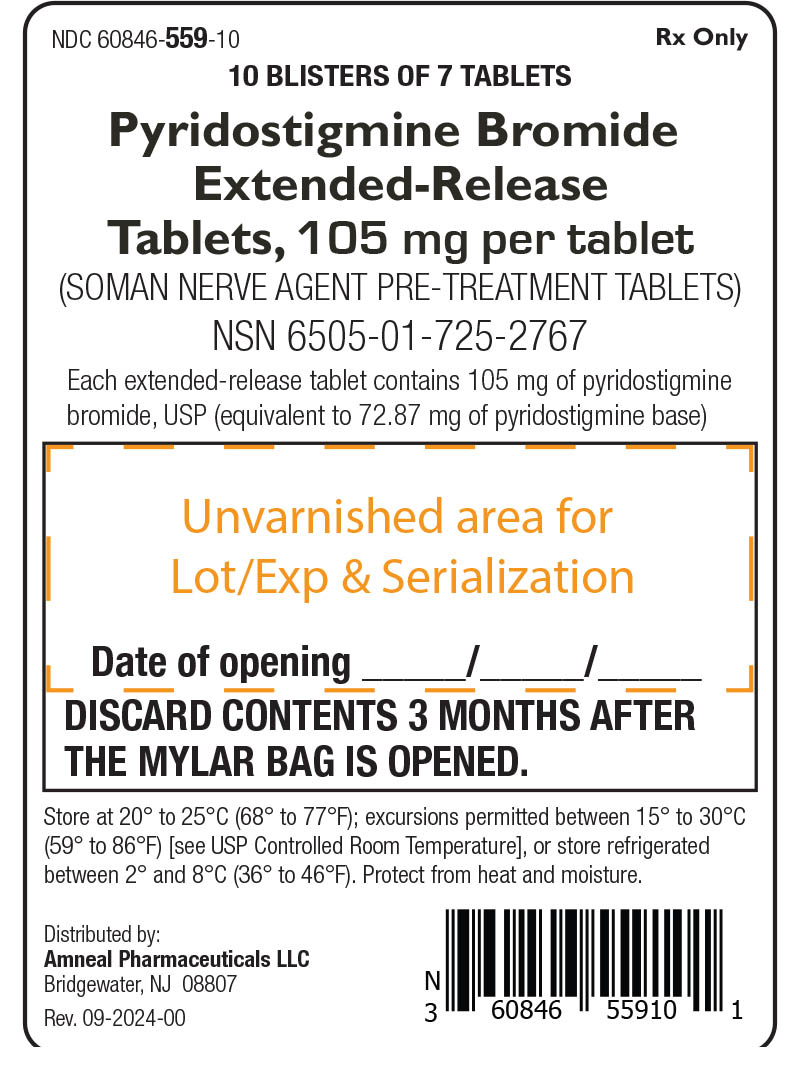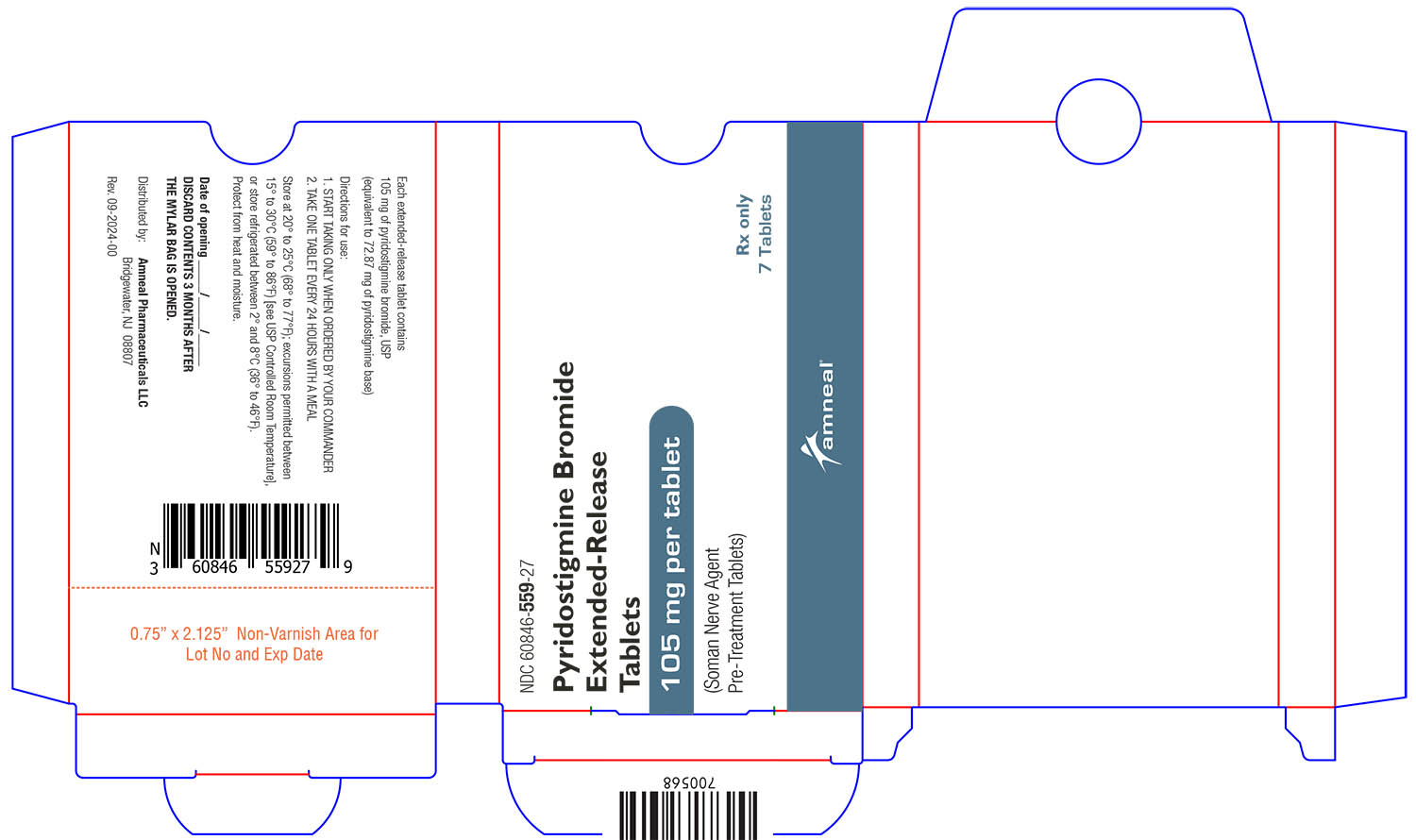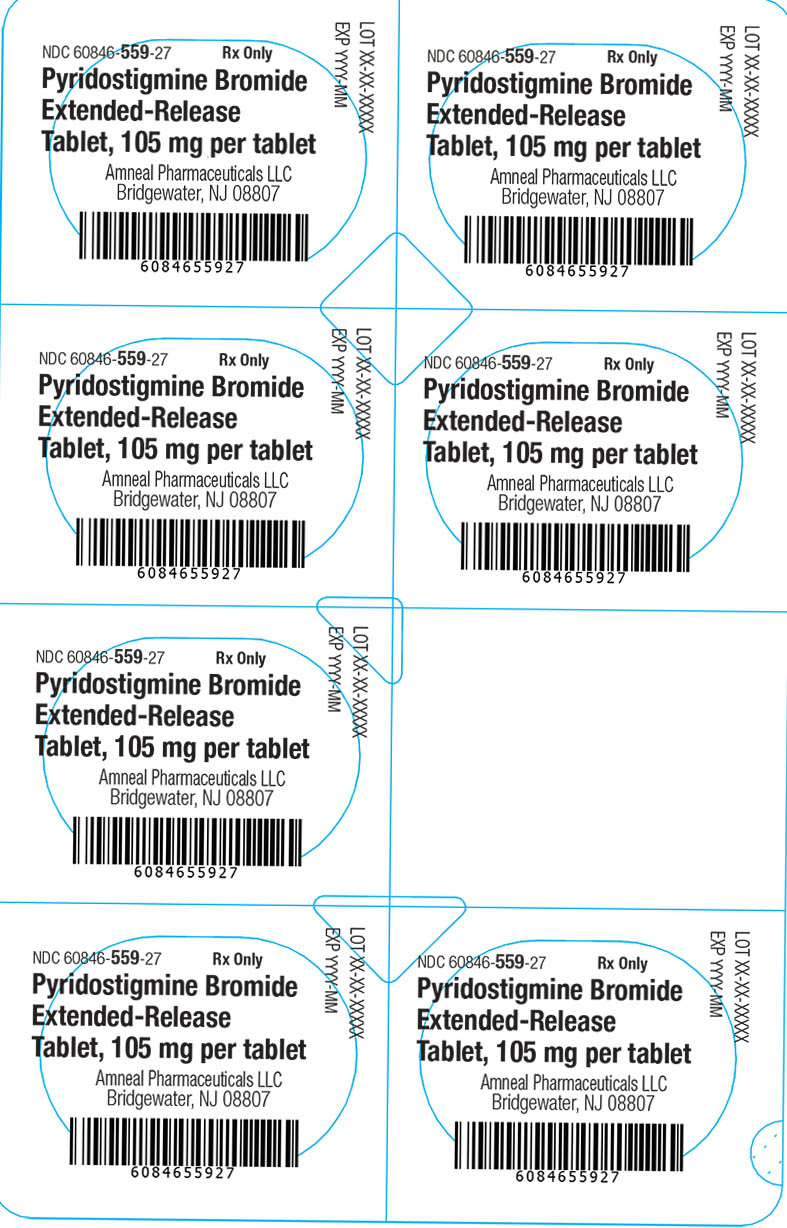 DRUG LABEL: Pyridostigmine bromide
NDC: 60846-559 | Form: TABLET, EXTENDED RELEASE
Manufacturer: Amneal Pharmaceuticals LLC
Category: prescription | Type: HUMAN PRESCRIPTION DRUG LABEL
Date: 20260122

ACTIVE INGREDIENTS: PYRIDOSTIGMINE BROMIDE 105 mg/1 1
INACTIVE INGREDIENTS: AMMONIUM METHACRYLATE; AMMONIA; FERROSOFERRIC OXIDE; CALCIUM CARBONATE; SILICON DIOXIDE; CROSPOVIDONE; HYDROXYPROPYL CELLULOSE, UNSPECIFIED; HYPROMELLOSES; FERRIC OXIDE RED; FERRIC OXIDE YELLOW; MAGNESIUM STEARATE; MANNITOL; PROPYLENE GLYCOL; SHELLAC; SODIUM BICARBONATE; SUCCINIC ACID; TALC; TITANIUM DIOXIDE; TRIETHYL CITRATE

HIGHLIGHTS OF PRESCRIBING INFORMATION

These highlights do not include all the information needed to use PYRIDOSTIGMINE BROMIDE EXTENDED-RELEASE TABLETS safely and effectively. See full prescribing information for PYRIDOSTIGMINE BROMIDE EXTENDED-RELEASE TABLETS.
PYRIDOSTIGMINE BROMIDE extended-release tablets, for oral use
Initial U.S. Approval: 1955

WARNING: RISKS WITH IMPROPER USE OF PYRIDOSTIGMINE BROMIDE

See full prescribing information for complete boxed warning.

After Exposure to Soman, Use Atropine and Pralidoxime

- Pyridostigmine bromide is for use as a pretreatment for exposure to soman nerve agent. Pyridostigmine bromide alone will not protect against exposure to soman. The efficacy of pyridostigmine bromide is dependent upon the rapid use of atropine and pralidoxime (2-PAM) after soman exposure. (2.1, 5.1)
  Always Use Protective Garment(s)
- Primary protection against exposure to chemical nerve agents is the wearing of protective garments. (2.1, 5.1)

Pyridostigmine Bromide as Pretreatment Only

If taken immediately before soman exposure (e.g., when the gas attack alarm is given) or at the same time as poisoning by soman, it is not expected to be effective and may exacerbate the effects of a sub-lethal exposure to soman. Do not take pyridostigmine bromide after exposure to soman. (2.1, 12.2)

RECENT MAJOR CHANGES

Contraindications (4) 09/2025

Warnings and Precautions (5.2) 09/2025

1 INDICATIONS AND USAGE

Pyridostigmine bromide is a cholinesterase inhibitor indicated for pretreatment against the lethal effects of soman nerve agent poisoning in adults. (1)

Pyridostigmine bromide is for use in conjunction with

- Protective garments, including a gas mask, and
- Immediate atropine and pralidoxime therapy at the first sign of nerve agent poisoning. (1)

2 DOSAGE AND ADMINISTRATION

- The recommended dosage is 105 mg orally once daily, started at least several hours prior to exposure to soman. Do not take on an empty stomach. Take with a medium-fat medium-calorie meal (e.g., meal with 650 calories, 40% fat) or a high-fat high-calorie meal (e.g., meal with 1,000 calories, 50% fat). Do not take with a low-fat low-calorie meal (e.g., meal with 400 calories, 25% fat) (2.2)
- At the first sign of soman nerve agent poisoning, discontinue pyridostigmine and administer atropine and pralidoxime immediately. (2.2)
- Evaluate use beyond 14 consecutive days in the context of the likelihood of soman exposure. (2.2)

3 DOSAGE FORMS AND STRENGTHS

Extended-release tablets: 105 mg (3)

4 CONTRAINDICATIONS

- Mechanical intestinal or urinary obstruction. (4)
- Known hypersensitivity to pyridostigmine or other anticholinesterase agents. (4)

5 WARNINGS AND PRECAUTIONS

- At the first sign of soman poisoning pyridostigmine must be stopped, and atropine and 2-PAM must be administered immediately. (5.1)
- Use with caution in persons with increased risk of anticholinergic reactions, such as persons with bronchial asthma, chronic obstructive pulmonary disease, bradycardia, cardiac arrhythmias, beta blocker treatment (increased risk of anticholinergic reactions). (5.2)
- Use with caution in persons with bromide sensitivity. (5.3)
- In case of serious adverse reactions, advise personnel to temporarily discontinue pyridostigmine and seek immediate medical attention. (5.4)

6 ADVERSE REACTIONS

Most common adverse reactions (≥ 3%) are diarrhea, abdominal pain, dysmenorrhea, and twitch. (6)

To report SUSPECTED ADVERSE REACTIONS, contact Amneal Pharmaceuticals at 1-877-835-5472 or FDA at 1-800-FDA-1088 or www.fda.gov/medwatch.

7 DRUG INTERACTIONS

- Mefloquine: Additive effect on gastrointestinal tract and atrial rate. (7.1)
- Anticholinesterase drugs for glaucoma treatment: Additive effect. (7.2)
- Narcotics: Exacerbation of bradycardia possible. (7.3)
- Depolarizing neuromuscular blocking agents: Increased effect. (7.4)
- Non-depolarizing neuromuscular blocking agents: Dose may need to be increased. (7.4)
- Aminoglycoside antibiotics, local and some general anesthetics, antiarrhythmic agents, and other drugs that interfere with neuromuscular transmission should be used cautiously, if at all. (7.4)
- Drugs converted to pantothenic acid (e.g., dexpanthenol): Additive effect. (7.5)

8 USE IN SPECIFIC POPULATIONS

Renal impairment: Increased risk of side effects; careful dose selection. In persons with renal impairment, renal function monitoring may be useful. (8.6)

FULL PRESCRIBING INFORMATION

WARNING: RISKS WITH IMPROPER USE OF PYRIDOSTIGMINE BROMIDE

After Exposure to Soman, Use Atropine and Pralidoxime

- Pyridostigmine bromide is for use as a pretreatment for exposure to soman nerve agent. Pyridostigmine bromide alone will not protect against exposure to soman. The efficacy of pyridostigmine bromide is dependent upon the rapid use of atropine and pralidoxime (2-PAM) after soman exposure [see Dosage and Administration (2.1) and Warnings and Precautions (5.1)].
  Always Use Protective Garment(s)
- Primary protection against exposure to chemical nerve agents is the wearing of protective garments including masks, hoods, and overgarments designed specifically for this use. Individuals must not rely solely upon pretreatment with pyridostigmine bromide and on the antidotes atropine and pralidoxime (2-PAM) to provide complete protection from poisoning by soman nerve agent [see Dosage and Administration (2.1)].
  Pyridostigmine Bromide as Pretreatment Only
- Pyridostigmine bromide must not be taken after exposure to soman. If pyridostigmine bromide is taken immediately before exposure (e.g., when the gas attack alarm is given) or at the same time as poisoning by soman, it is not expected to be effective and may exacerbate the effects of a sub-lethal exposure to soman [see Clinical Pharmacology (12.2)].

FOR MILITARY MEDICAL USE ONLY

1 INDICATIONS AND USAGE

Pyridostigmine bromide is indicated for pretreatment against the lethal effects of soman nerve agent poisoning in adults. Pyridostigmine bromide is intended for use in conjunction with protective garments, including a mask. At the first sign of nerve agent poisoning, pyridostigmine bromide should be stopped, and atropine and pralidoxime therapy started immediately.

The evidence for the effectiveness of pyridostigmine bromide as pretreatment against soman-induced toxicity was derived from animal studies alone [see Clinical Studies (14)].

FOR MILITARY MEDICAL USE ONLY

2 DOSAGE AND ADMINISTRATION

2.1 Important Administration Information

For Military Medical Use Only.

Treatment and Protection for Soman Exposure

Pyridostigmine bromide is for use as a pretreatment for exposure to soman nerve agent (see Treatment Timing). Pyridostigmine bromide alone will not protect against exposure to soman.

Atropine and Pralidoxime

The efficacy of pyridostigmine bromide is dependent upon the rapid use of atropine and pralidoxime (2-PAM) after soman exposure.

Primary Protection

The primary protection against exposure to chemical nerve agents consists of wearing protective garments including masks, hoods, and overgarments designed specifically for this use.

Do not rely solely upon pretreatment with pyridostigmine bromide and the antidotes atropine and pralidoxime to provide complete protection from poisoning by soman nerve agent.

Treatment Timing

Pyridostigmine bromide is to be administered as pretreatment before exposure to soman nerve agent [see Dosage and Administration (2.2)]. If pyridostigmine bromide is taken immediately before exposure (e.g., when the gas attack alarm is given) or at the same time as poisoning by soman, it is not expected to be effective and may exacerbate the effects of a sublethal exposure to soman [see Clinical Pharmacology (12.2)]. Do not take pyridostigmine bromide after exposure to soman.

Administration with Food

Take pyridostigmine bromide 105 mg extended-release tablets with either a medium fat, medium calorie or high fat, high calorie meal to maintain efficacious pyridostigmine levels [see Dosage and Administration (2.2) and Clinical Pharmacology (12.3)].

Administration with Alcohol

Pyridostigmine bromide 105 mg extended-release tablets should not be taken with alcohol [see Clinical Pharmacology (12.3)].

2.2 Recommended Dosage, Administration, and Duration

Dosage

The recommended dosage of pyridostigmine bromide is 105 mg orally once daily with food, started at least several hours prior to exposure to soman. Do not take on an empty stomach. Take with a medium-fat medium-calorie meal (e.g., meal with 650 calories, 40% fat) or a high-fat high-calorie meal (e.g., meal with 1,000 calories, 50% fat). Do not take with a low-fat low-calorie meal (e.g., meal with 400 calories, 25% fat) [see Clinical Pharmacology (12.3)].

Timing and Duration of Treatment

Timing

Pyridostigmine bromide is a pretreatment for exposure to soman nerve agent.

There is no known advantage to taking pyridostigmine bromide just prior to, or concurrent with, soman exposure. According to the mechanism of action of pyridostigmine bromide [see Clinical Pharmacology (12.1, 12.2)], pyridostigmine bromide is effective when it is given sufficiently in advance of soman poisoning to provide a pool of protected enzyme. Therefore, it is expected that pyridostigmine bromide will not be effective if administered just prior to or during exposure to soman.

Duration

At the first sign of nerve agent poisoning, discontinue pyridostigmine bromide and administer pretreatment with atropine and pralidoxime immediately [see Warnings and Precautions (5.1)].

The benefits and risks of use beyond 14 consecutive days have not been definitively established; therefore, evaluate continued use beyond 14 consecutive days in the context of the likelihood of exposure to soman nerve agent.

Missed Dose

If a dose is missed, take the missed dose as soon as possible. Resume dosing at 24-hour intervals from the time the missed dose was taken. Do not take double or extra doses.

3 DOSAGE FORMS AND STRENGTHS

Extended-Release Tablets: 105 mg, peach, oval, coated, unscored, biconvex tablets imprinted with “A2 463” on one side and plain on the other side. A hole may be visible on one side of the tablet.

4 CONTRAINDICATIONS

Pyridostigmine bromide extended-release tablets are contraindicated in patients with:

- Mechanical intestinal or urinary obstruction
- Known hypersensitivity to pyridostigmine or other anticholinesterase agents

5 WARNINGS AND PRECAUTIONS

5.1 Risk of Improper Use of Pyridostigmine Bromide

Risk of Not Stopping Pyridostigmine Bromide and Using Atropine and Pralidoxime in the Event of Soman Exposure

Pyridostigmine bromide is for use as pretreatment for exposure to soman nerve agent and must not be taken after exposure to soman nerve agent [see Dosage and Administration (2.1, 2.2)]. Pyridostigmine bromide pretreatment offers no benefit against the nerve agent soman unless the nerve agent antidotes, atropine and pralidoxime (2-PAM), are administered once symptoms of poisoning appear.

Discontinue pyridostigmine at the first sign of nerve agent poisoning because it may exacerbate the effects of a sub-lethal exposure to soman if taken immediately before exposure (e.g., when the gas attack alarm is given) or at the same time as poisoning by soman [see Clinical Pharmacology (12.2)]. Signs of nerve agent poisoning can include runny nose; watery eyes; small, pinpoint pupils; eye pain; blurred vision; drooling and excessive sweating; cough; chest tightness; rapid breathing; diarrhea; increased urination; confusion; drowsiness; weakness; headache; nausea, vomiting, and/or abdominal pain; slow or fast heart rate; and/or abnormally low or high blood pressure.

Risk of Not Wearing Protective Garments

Pyridostigmine bromide is not the primary protection against exposure to soman nerve agent.

The primary protection against exposure to chemical nerve agents is the wearing of protective garments including masks, hoods, and overgarments designed specifically for this use. Individuals must not rely solely upon pretreatment with pyridostigmine bromide and on the antidotes, atropine and pralidoxime (2-PAM), to provide complete protection from poisoning by soman nerve agent.

5.2 Increased Risk of Anticholinergic Adverse Reactions in Individuals with Certain Conditions

Pulmonary Conditions

Drugs that increase cholinergic activity, including pyridostigmine bromide, should be used with caution in persons with bronchial asthma or chronic obstructive pulmonary disease.

Cardiovascular Conditions

Because pyridostigmine bromide increases cholinergic activity, it may have vagotonic effects on heart rate, which can lead to bradycardia or cardiac arrhythmias.

Genitourinary Tract or Gastrointestinal Tract Obstruction

Drugs that increase cholinergic agents, including pyridostigmine bromide, could cause symptoms in persons susceptible to genitourinary tract or gastrointestinal tract obstruction.

Conditions Treated with Beta Adrenergic Receptor Blockers

Pyridostigmine bromide should be used with caution in people being treated for hypertension or glaucoma with beta adrenergic receptor blockers [see Drug Interactions (7.2)].

5.3 Use in Bromide-Sensitive Individuals

Caution should be taken when administering pyridostigmine bromide to individuals with known bromide sensitivity. As with any compound containing bromide, a skin rash may be observed in bromide-sensitive patients, which usually subsides promptly upon discontinuance of the medication. The risks and benefits of administration must be weighed against the potential for rash or other adverse reactions in these individuals.

5.4 Serious Adverse Reactions, Such as Difficulty Breathing, Severe Dizziness, Loss of Consciousness

Pyridostigmine bromide can cause serious adverse reactions such as difficulty breathing, severe dizziness, or loss of consciousness. If these adverse reactions occur, patients should temporarily discontinue use of pyridostigmine bromide and seek immediate medical attention. Personnel should report serious adverse events to their commander and responsible medical officer.

6 ADVERSE REACTIONS

The following serious adverse reactions are discussed elsewhere in the labeling:

- Risk of Improper Use of Pyridostigmine Bromide [see Warnings and Precautions (5.1)]
- Individuals at Increased Risk of Anticholinergic Adverse Reactions [see Warnings and Precautions (5.2)]
- Use in Bromide-Sensitive Individuals [see Warnings and Precautions (5.3)]

Serious Adverse Reactions, Such as Difficulty Breathing, Severe Dizziness, Loss of Consciousness [see Warnings and Precautions (5.4)]

6.1 Clinical Trials Experience

Because clinical trials are conducted under widely varying conditions, adverse reaction rates observed in the clinical trials of a drug cannot be directly compared to rates in the clinical trials of another drug and may not reflect the rates observed in practice.

The adverse reactions to pyridostigmine bromide are typically of two varieties: muscarinic and nicotinic. Muscarinic adverse reactions include abdominal cramps, bloating, flatulence, diarrhea, emesis, increased peristalsis, nausea, hypersalivation, urinary incontinence, increased bronchial secretion, diaphoresis, miosis, and lacrimation. Nicotinic adverse reactions are comprised chiefly of muscle cramps, fasciculations, and weakness.

In a controlled study of 90 healthy volunteers comparing immediate-release pyridostigmine bromide 30 mg every 8 hours, which provides exposures comparable to pyridostigmine bromide 105 mg extended-release tablets once daily, to placebo for 21 days, the adverse reactions that were reported in 2% or more of subjects is included in Table 1. The most common adverse reactions (≥ 3%) are diarrhea, abdominal pain, dysmenorrhea, and twitch.

Table 1: Incidence of Adverse Reactions ≥ 2%

Adverse Reaction | Pyridostigmine N = 60; % | Placebo N = 30; %
Diarrhea | 7 | 0
Abdominal Pain | 7 | 0
Dysmenorrhea | 5 | 0
Twitch | 3 | 0
Myalgia | 2 | 0
Dry Skin | 2 | 0
Urinary Frequency | 2 | 0
Epistaxis | 2 | 0
Amblyopia | 2 | 0
Hypesthesia | 2 | 0
Neck pain | 2 | 0

Other less common adverse reactions seen during controlled and uncontrolled clinical trials for pyridostigmine include the following:

- Pulmonary: Exacerbation of acute bronchitis and asthma
- Cardiovascular: Elevated blood pressure, decreased heart rate (4-6 beats per minute), chest tightness
- Eyes: Change in vision, eye pain
- Neurologic: Headache, hypertonia, difficulty in concentrating, confusion, disturbed sleep, tingling of extremities, numbness of the tongue
- Skin: Increased sweating, rash, alopecia
- Digestive: Vomiting, borborygmi, nausea, bloating, flatulence
- General: Warm sensation, lethargy/drowsiness, depressed mood

During safety studies at the recommended dosage of immediate release pyridostigmine bromide 30 mg every 8 hours, which provides exposures comparable to pyridostigmine bromide 105 mg extended-release tablets once daily, there were two reports of loss of consciousness, one of which also included urinary and fecal incontinence, stiffness of the upper torso and arms, post-syncopal skin pallor, post-syncopal confusion, and post-syncopal weakness (suggesting a seizure event).

Central Nervous System Adverse Reactions

Pyridostigmine bromide is a quaternary ammonium compound and does not readily cross the blood-brain barrier. Compared to the peripheral effects of pyridostigmine bromide, central nervous system manifestations are less frequent and less serious, primarily consisting of headache and vertigo, with minor and clinically insignificant changes in heart rate, blood pressure, and respiratory function.

7 DRUG INTERACTIONS

7.1 Mefloquine

Concomitant use of mefloquine and pyridostigmine bromide may have additive effects on the gastrointestinal tract, the most common of which is loose bowels. Additive effects on the atrial rate may also occur with concomitant use of mefloquine and pyridostigmine bromide.

7.2 Other Anticholinesterase Drugs

Concomitant use of anticholinesterase drugs used in the treatment of glaucoma and pyridostigmine bromide may have an additive effect that may cause or exacerbate problems with night vision.

7.3 Narcotics

The bradycardia associated with the use of narcotics may exacerbate pyridostigmine-induced bradycardia.

7.4 Drugs that Interfere with Neuromuscular Transmission

Particular caution should be observed in the administration of depolarizing neuromuscular blocking agents (e.g., succinylcholine) during surgery since the degree of neuromuscular blockade that ensues may be enhanced by previously administered pyridostigmine bromide. Doses of non-depolarizing neuromuscular blocking agents (e.g., pancuronium bromide) may need to be increased in patients previously administered pyridostigmine bromide. Atropine antagonizes the muscarinic effects of pyridostigmine bromide, and this interaction is utilized to counteract the muscarinic symptoms of pyridostigmine bromide toxicity. Anticholinesterase agents are sometimes effective in reversing neuromuscular block induced by aminoglycoside antibiotics. However, aminoglycoside antibiotics, local and some general anesthetics, antiarrhythmic agents, and other drugs that interfere with neuromuscular transmission should be used cautiously, if at all, during treatment with pyridostigmine bromide.

7.5 Drugs Converted to Pantothenic Acid

Concomitant use of drugs that are converted to pantothenic acid in vivo (e.g., dexpanthenol) and pyridostigmine bromide may have additive effects by increasing production of acetylcholine.

8 USE IN SPECIFIC POPULATIONS

8.1 Pregnancy

Risk Summary

Available data from case reports and case series over decades of use with pyridostigmine bromide have not identified a drug-associated risk of major birth defects, miscarriage, or other adverse maternal or fetal outcomes. Treatment with pyridostigmine bromide for soman nerve agent poisoning during pregnancy should not be delayed because exposure to soman during pregnancy may increase the risk of maternal and fetal morbidity and mortality.

In animal studies, oral administration of pyridostigmine during organogenesis resulted in adverse developmental effects (increased embryofetal mortality and fetal structural abnormalities), at clinically relevant doses (see Data).

The background risk for major birth defects and miscarriage for the indicated population is unknown. All pregnancies have a background risk of birth defect, loss, or other adverse outcomes. In the U.S. general population, the estimated background risk of major birth defects and miscarriage in clinically recognized pregnancies is 2% to 4% and 15% to 20%, respectively.

Data

Animal Data

Oral administration of pyridostigmine to pregnant rats during organogenesis resulted in increases in embryofetal deaths and incidences of fetal skeletal variations at the highest dose tested (30 mg/kg/day), which was also maternally toxic. A slight increase in the incidence of hydronephrosis was observed at all dose levels (lowest dose tested was 3 mg/kg/day). A no-effect dose for adverse effects on embryofetal development in the rat was not identified. The lowest dose tested (3 mg/kg/day) is less than the recommended human dose (105 mg) on a body surface area (mg/m^2) basis.

Oral administration of pyridostigmine to pregnant rabbits during organogenesis resulted in an increase in the incidence of visceral variations at the highest dose tested (45 mg/kg/day), which was also maternally toxic. An increased incidence of blood vessel variations was observed at all doses (lowest dose tested was 5 mg/kg/day). A no-effect dose for adverse effects on embryofetal development in the rabbit was not identified. The lowest dose tested (5 mg/kg/day) is less than the recommended human dose on a body surface area (mg/m2) basis.

8.2 Lactation

Risk Summary

Pyridostigmine bromide is present in human milk. Based on limited data, pyridostigmine bromide was not detected in the plasma of infants who were breastfed by mothers taking pyridostigmine bromide. There are no data on the effects on milk production. The developmental and health benefits of breastfeeding should be considered along with the mother’s clinical need for pyridostigmine bromide and any potential adverse effects on the breastfed infant from pyridostigmine bromide or from the underlying maternal condition.

8.4 Pediatric Use

Safety and effectiveness in pediatric patients have not been established.

8.5 Geriatric Use

Clinical studies of pyridostigmine bromide did not contain sufficient numbers of subjects aged 65 and over to determine whether they respond differently than younger subjects. In general, dose selection for an elderly patient should be cautious, reflecting the greater frequency of decreased hepatic, renal, or cardiac function, and of concomitant disease or other drug therapy.

This drug is known to be substantially excreted by the kidney, and the risk of toxic reactions to this drug may be greater in patients with impaired renal function. Because elderly patients are more likely to have decreased renal function [see Clinical Pharmacology (12.3)], care should be taken in dose selection, and it may be useful to monitor renal function.

8.6 Renal Impairment

This drug is known to be substantially excreted by the kidney, and the risk of toxic reactions to this drug may be greater in patients with impaired renal function. Caution should be observed, and dosage be selected carefully, when administering pyridostigmine bromide to patients with impaired renal function. [see Clinical Pharmacology (12.3)]. It may be useful to monitor renal function.

10 OVERDOSAGE

Overdosage of pyridostigmine bromide may result in cholinergic crisis, a state characterized by increasing muscle weakness that, through involvement of the muscles of respiration, may lead to death. Overdosage with pyridostigmine bromide must be differentiated from the acute manifestations of nerve agent poisoning, which may also be characterized by a cholinergic crisis.

Extremely high doses of pyridostigmine bromide may also produce central nervous system (CNS) symptoms of agitation, restlessness, confusion, visual hallucinations, and paranoid delusions. Electrolyte abnormalities, possibly resulting from high serum bromide concentrations, also have been reported. Death may result from cardiac arrest or respiratory paralysis and pulmonary edema.

In the treatment of pyridostigmine bromide overdosage, maintaining adequate respiration is of primary importance. Tracheostomy, bronchial aspiration, and postural drainage may be required to maintain an adequate airway; respiration can be assisted mechanically if required. Supplemental oxygen may be necessary. Pyridostigmine bromide should be discontinued immediately and 1 mg to 4 mg of atropine sulfate administered intravenously. Additional doses of atropine may be given every 5 to 30 minutes as needed to control muscarinic symptoms. Atropine overdosage should be avoided, as tenacious secretions and bronchial plugs may result. It should be kept in mind that unlike muscarinic effects, the skeletal muscle effects and consequent respiratory paralysis (nicotinic effects), which can occur following pyridostigmine overdosage, are not alleviated by atropine.

11 DESCRIPTION

Pyridostigmine bromide is an orally active, reversible cholinesterase inhibitor. Pyridostigmine bromide is a white or almost white, crystalline, deliquescent powder, very soluble in water and alcohol, and practically insoluble in ether.

CAS registration number is 101-26-8.

Pyridostigmine bromide has a molecular formula of C9H13BrN2O2, with a molecular weight of 261.12. Its chemical name is 3-hydroxy-1-methylpyridinium bromide dimethylcarbamate, and its structural formula is:

Pyridostigmine bromide extended-release tablets contain 105 mg of pyridostigmine bromide (equivalent to 72.87 mg of pyridostigmine base) for oral administration. The inactive ingredients included in the tablet formula are ammonia methacrylate copolymer, ammonium hydroxide, black iron oxide, calcium carbonate, colloidal silicon dioxide, crospovidone, hydroxypropyl cellulose, hypromellose, iron oxide red, iron oxide yellow, magnesium stearate, mannitol, propylene glycol, shellac glaze, sodium bicarbonate, succinic acid, talc, titanium dioxide, and triethyl citrate.

12 CLINICAL PHARMACOLOGY

12.1 Mechanism of Action

Pyridostigmine is a reversible cholinesterase inhibitor.

12.2 Pharmacodynamics

The mechanism of soman-induced death is reasonably well understood. Death is believed to result primarily from respiratory failure due to irreversible inhibition of the enzyme acetylcholinesterase and the consequent increase in the level of the neurotransmitter acetylcholine 1) at nicotinic receptors at the neuromuscular junction, resulting in pathological stimulation and ultimate failure of the muscles of respiration, 2) at muscarinic receptors in secretory glands and smooth muscle, resulting in excessive respiratory secretions and bronchoconstriction, and 3) at cholinergic receptors in the brain, resulting in central respiratory depression.

The effect of pyridostigmine is presumed to result from its reversible inhibition of a critical number of acetylcholinesterase active sites in the peripheral nervous system, protecting them from irreversible inhibition by soman. (Pyridostigmine bromide is not thought to enter the brain in significant amounts.) When the pyridostigmine bromide-induced inhibition of the enzyme is subsequently reversed, there is a small residual amount of enzyme activity that is adequate to sustain life (provided atropine and 2-PAM are subsequently administered). An implication of this presumed mechanism is that it is not helpful to give pyridostigmine bromide either just before or during exposure to soman [see Dosage and Administration (2.1, 2.2)].

12.3 Pharmacokinetics

Absorption

Pyridostigmine bromide is poorly absorbed from the gastrointestinal tract with an absolute bioavailability of 10% to 20%. Following a single oral dose of 105 mg pyridostigmine bromide extended-release tablet in the fed state, the median Tmax was 10.00 (5.00 – 18.00) hours with medium fat, medium calorie meal and 16.00 (5.00 – 20.00) hours with high fat, high calorie meal.

Effect of Food

The pharmacokinetic parameters of pyridostigmine bromide 105 mg extended-release tablets showed a significant food effect in regard to fasted vs. fed and to the types of meals consumed. Single oral doses were administered to healthy volunteers (N=32) under four different conditions as described below:

- Fasted state
- Low Fat, Low Calorie (LFLC): ~450-500 Kcal; fat ~25%
- Medium Fat, Medium Calorie (MFMC): ~600-650 Kcal; fat ~40%
- High Fat, High Calorie (HFHC): ~800-1000 Kcal; fat ~50%

Following administration of 105 mg pyridostigmine bromide extended-release tablets, the oral bioavailability is greater when taken with food than when taken in the fasted state. Under fed conditions, the exposure was greatest with HFHC meal compared to LFLC meal. Peak of exposure and overall exposure were similar with MFMC and HFHC meals.

The exposure is greatest following a HFHC meal, with a 55% higher Cmax and 231% higher AUC compared to the fasted state; a 32% higher Cmax and 89% higher AUC compared to LFLC meal.

Compared to HFHC and MFMC meal, the pyridostigmine exposure is lower during the second half of the proposed 24-hour dosing interval under fasted or LFLC meal condition.

Table 2 and Figure 1 below show pyridostigmine concentration-time profile and summary of pharmacokinetic (PK) parameters, respectively, after single dose administration of 105 mg pyridostigmine bromide extended-release tablet under fasted condition, or with food of different fat and calorie contents [see Dosage and Administration (2.1, 2.2)].

Figure 1: Effect of Food on Concentration-Time Profile of Pyridostigmine Bromide 105 mg Extended-Release Tablets

LFLC=low fat, low calorie; MFMC=medium fat, medium calorie; HFHC=high fat, high calorie

Table 2: Summary of Food Effect on PK Parameters of Pyridostigmine Bromide 105 mg Extended-Release Tablets

PK Parameters | Fasted | Low Fat/; Low Calorie | Medium Fat/; Medium Calorie | High Fat/; High Calorie
PK Parameters | Mean [SD] | Mean [SD] | Mean [SD] | Mean [SD]
Cmax (ng/mL) | 9.30 [4.16] | 10.91 [3.55] | 13.76 [3.72] | 14.43 [3.18]
Tmax* (hours) | 4.00 [1.00 – 5.00] | 5.00 [4.00 – 20.00] | 10.0 [5.00 – 18.00] | 16.00 [5.00 – 20.00]
AUClast (ng.h/L) | 68.90 [33.31] | 120.40 [82.38] | 205.11 [81.09] | 228.15 [59.99]
AUCinf; (ng.h/L) | 77.22 [40.5] | 136.45 [88.53] | 215.81 [81.30] | 236.18 [61.35]
T1/2* (hours) | 6.71 [4.15] | 7.39 [5.14] | 5.43 [1.40] | 5.31 [1.51]

* Arithmetic mean (standard deviation) except Tmax where it is median (minimum, maximum).

Effect of Alcohol

In an in vitro dissolution study where pyridostigmine bromide 105 mg extended-release tablets were assessed in the presence of 0.1 mol/L standardized hydrochloric acid solution (0.1 N HCl) with 0%, 5%, 20%, and 40% ethanol demonstrated that 20% and 40% alcohol can cause faster release of pyridostigmine

[see Dosage and Administration (2.1)].

Distribution

The volume of distribution was about 19 ± 12 liters, indicating that pyridostigmine bromide distributes into tissues. No information on protein binding of pyridostigmine bromide is available.

Elimination

Metabolism

Pyridostigmine bromide undergoes hydrolysis by cholinesterases and is metabolized in the liver.

Excretion

Pyridostigmine bromide is excreted in the urine as both unchanged drug and its metabolites. The systemic clearance of pyridostigmine bromide is 830 mL/min and the elimination half-life of pyridostigmine bromide is approximately 5.6 hours.

Specific Populations

Patients with Renal Impairment

In anephric patients (n = 4), the elimination half-life increased 3-fold and the systemic clearance decreased by 75% [see Use in Specific Populations (8.6)].

Patients with Hepatic Impairment

No information is available on the pharmacokinetics of pyridostigmine bromide in hepatic impaired patients.

Male and Female Patients

The clearance of pyridostigmine bromide is not influenced by gender.

Geriatric Patients

In a pyridostigmine bromide study in elderly subjects (71 to 85 years of age), the elimination half-life of pyridostigmine and volume of distribution (central and steady-state) were comparable with younger subjects (21 to 51 years of age). However, the systemic plasma clearance was 30% lower in the elderly [see Use in Specific Populations (8.5)].

13 NONCLINICAL TOXICOLOGY

13.1 Carcinogenesis and Mutagenesis and Impairment of Fertility

Carcinogenicity

Studies to evaluate the carcinogenic potential of pyridostigmine bromide have not been conducted.

Mutagenicity

Pyridostigmine bromide was negative in in vitro (bacterial reverse mutation, mammalian gene mutation in Chinese hamster ovary (CHO) cells, clastogenicity in CHO cells) and in vivo (mouse micronucleus) assays. Pyridostigmine bromide was mutagenic and clastogenic in an in vitro mammalian gene mutation assay in mouse lymphoma cells, in the presence of metabolic activation.

Impairment of Fertility

Pyridostigmine bromide did not impair fertility in male or female rats given oral doses of up to 45 mg/kg/day (5 times the recommended human daily dose (105 mg) on a mg/m^2 basis) beginning at 10 (males) or 2 (females) weeks prior to mating.

14 CLINICAL STUDIES

The effectiveness of pyridostigmine bromide as a pretreatment against the lethal effects of soman nerve agent poisoning has not been determined in humans because adequate and well-controlled field trials have not been feasible and inducing soman nerve agent poisoning in humans to study the drug’s efficacy is not ethical. Therefore, the effectiveness of pyridostigmine bromide as a pretreatment for against the lethal effects of soman nerve agent poisoning was established based on the results of the following adequate and well-controlled animal efficacy studies.

Evidence of the effectiveness of pyridostigmine bromide as a pretreatment for soman poisoning was obtained from studies in animals alone, because it is unethical to perform such studies in humans. While the results of these animal studies cannot be extrapolated to humans with certainty, the extrapolation is supported by the reasonably well understood pathophysiologic mechanisms of the toxicity of soman and the mechanism of the protective effect of pyridostigmine bromide pretreatment, as examined in various animal species. In addition, the results of these animal studies establish that pyridostigmine bromide is reasonably likely to produce clinical benefit in humans. The section below explains the current understanding of the mechanism of soman toxicity and the beneficial effect of pyridostigmine bromide pretreatment, as well as the basis for extrapolating the animal findings to humans.

Pyridostigmine bromide pretreatment has been shown in animals to decrease the lethality of the soman nerve agent, provided atropine and pralidoxime (2-PAM) are administered immediately after exposure to soman.

Rhesus monkeys were given oral doses of pyridostigmine bromide every 8 hours for a total of 6 doses and were challenged with soman given intramuscularly 5 hours after the last pyridostigmine bromide dose. Two dosage groups of pyridostigmine bromide were used: a low-dose group given 1.2 mg/kg for all 6 doses and a high-dose group given 1.2 and 1.8 mg/kg for the first and second doses, respectively, and 2.4 mg/kg for the final 4 doses. These animals were also given atropine and 2-PAM after exposure to soman. An untreated control group and a group given atropine and 2-PAM (but not pyridostigmine bromide) were also used. The primary endpoint in this study was a decrease in the lethality of soman expressed as an increase in the LD50 (the dose of soman that killed 50% of the animals). The atropine/2-PAM control group showed a small but statistically significant 1.6-fold increase in the soman LD50 compared to the untreated control group. The groups given pyridostigmine bromide as well as atropine and 2-PAM showed increases in the soman LD50 of at least 40-fold compared to the untreated control group and at least 25-fold compared to the atropine/2-PAM group. The two dose levels of pyridostigmine bromide showed similar effectiveness.

Additional studies in rhesus monkeys and guinea pigs also showed effectiveness of pyridostigmine bromide (in the presence of post-soman administration of atropine and 2-PAM). The magnitude of effect in guinea pigs was smaller than that in monkeys (soman LD50 increased 4 to 7-fold compared to untreated control and 2- to 4-fold compared to atropine/2-PAM alone).

Pyridostigmine bromide produced only small and inconsistent effects in studies in rats, mice, and rabbits. It is thought that the effect of pyridostigmine bromide in rats and mice is masked by high blood levels of the enzyme carboxylesterase, which eliminates soman from blood and makes those species highly resistant to soman. In a study in which rats were given an inhibitor of carboxylesterase, pretreatment with pyridostigmine bromide plus atropine and 2-PAM increased the LD50 of soman 8.5-fold compared to untreated controls. Humans have little or no carboxylesterase in blood.

Animal studies have shown that pyridostigmine bromide pretreatment was effective only when animals were given atropine and 2-PAM after exposure to soman.

16 HOW SUPPLIED

16.1 How Supplied

Pyridostigmine bromide extended-release tablets, 105 mg, are supplied as oval, peach, coated, unscored, biconvex tablets imprinted with “A2 463” on one side and plain on the other side. A hole may be visible on one side of the tablet.

They are available as follows:

Mylar bag containing 10 blister cartons. Each blister carton contains seven (7) tablets.

NDC 60846-559-10.

16.2 Storage and Handling

Store at 20°C to 25°C (68°F to 77°F); excursions permitted between 15°C to 30°C (59°F to 86°F) [see USP Controlled Room Temperature], or store refrigerated between 2°C and 8°C (36°F to 46°F). Protect from heat and moisture. Discard contents of blister pack 3 months after the mylar bag is opened.

17 PATIENT COUNSELING INFORMATION

Advise the patient to read the FDA-approved patient labeling (Patient Information).

Indication and Conditions of Use

Advise personnel of the following:

- Pyridostigmine bromide is approved as a pretreatment against the lethal effects of the chemical nerve agent soman (GD). Pyridostigmine bromide has not been approved for use against other chemical nerve agents including Sarin (GB), Tabun (GA), and VX [see Indications and Usage (1)]. The approval is based on safety studies in humans and effectiveness studies conducted in animals. It is not ethical to do effectiveness studies in humans. Human studies would require exposing people to the deadly effects of nerve agents, risking poisoning them or even killing them. Studies in monkeys and guinea pigs show that pretreatment with pyridostigmine bromide makes the antidotes (atropine and 2-PAM) work better against soman (GD) [see Clinical Studies (14)].
- The main protection against chemical weapons is the chemical protective mask and battle dress overgarments [see Dosage and Administration (2.1, 2.2) and Warnings and Precautions (5.1)].
- Pyridostigmine bromide is used as a pretreatment against a soman nerve agent attack. Based on the animal studies, it is thought that any potential benefits from use of pyridostigmine bromide occur only if:

1. It is taken at least several hours before, but not right before, exposure to the nerve agent soman. If it is taken right before (when the nerve gas attack alarm is given) or during nerve agent exposure, it may not work and may make the effects of soman worse.
2. Atropine and 2-PAM are used when symptoms of nerve agent poisoning occur. [see Dosage and Administration (2.1, 2.2)].

Dosage and Administration [see Dosage and Administration (2.1, 2.2)]

Inform personnel of the following:

- The chain of command will instruct when it is time to take pyridostigmine bromide, based on the threat of exposure to soman nerve agents.
- Take one tablet orally once daily, with food, until the chain of command instructs to stop taking pyridostigmine bromide. Do not take on an empty stomach. Take with a medium fat, medium calorie meal (e.g., meal with 650 calories, 40% fat) or a high fat, high calorie meal (e.g., meal with 1,000 calories, 50% fat). Do not take the tablet with a low fat, low calorie meal (e.g., meal with 400 calories, 25% fat).
- Take pyridostigmine bromide only as prescribed.
- If a dose is missed, take the missed dose as soon as possible. Do not take double or extra doses.
- There is no known advantage to taking extra pyridostigmine bromide right before soman exposure.
- Discontinue pyridostigmine bromide after nerve agent exposure has occurred, and instead:

- Persons experiencing most or all of the MILD symptoms of nerve agent poisoning (runny nose; watery eyes; small, pinpoint pupils; eye pain; blurred vision; drooling and excessive sweating; cough; chest tightness; rapid breathing; diarrhea; increased urination; confusion; drowsiness; weakness; headache; nausea, vomiting, and/ or abdominal pain; slow or fast heart rate; and/or abnormally low or high blood pressure) should IMMEDIATELY AVOID INHALATION (hold their breath) AND PUT ON THEIR PROTECTIVE MASK.
- Then atropine and 2-PAM must be administered.

- Contact their unit medical officer if adverse reactions from pyridostigmine bromide continue and limit duty performance.

Risks in Individuals with Certain Conditions [see Contraindications (4), Warnings and Precautions (5.2), and Use in Specific Populations (8.1)]

Instruct personnel to inform their healthcare provider before taking pyridostigmine bromide if they:

- Are pregnant
- Have asthma
- Are allergic to bromide, pyridostigmine, or anticholinesterase drugs
- Take a beta blocker (a medicine to treat, e.g., high blood pressure)
- Have high eye pressure (glaucoma)
- Have any other medical condition, including heart problems, genitourinary or gastrointestinal obstruction, or reflux esophagitis (GERD)

Collection of Information

The Department of Defense (DoD) may collect information on the use of pyridostigmine bromide to help decide how best to protect deployed forces in the future. Information that identifies individual persons will remain confidential. However, the FDA may review any data collected by DoD for the purpose of evaluating pyridostigmine bromide.

Questions and Requests for Information

Questions about personnel rights and welfare should be directed to the unit medical officer or e-mailed to usamrmcregulatoryaffairs@mail.mil.

Personnel can receive information about pyridostigmine bromide from unit medical officers or medics. Questions about pyridostigmine bromide can also be e-mailed directly to the US Army Medical Research and Materiel Command at address usarmy.detrick.medcom-usammda.mbx.usamrmc-regulatory-affairs@mail.mil.

Distributed by:

Amneal Pharmaceuticals LLC

Bridgewater, NJ 08807

Rev. 10-2025-01

Important Information

Rx Only

PYRIDOSTIGMINE BROMIDE extended-release tablets 105 mg

Protection Against Soman Nerve Agent Poisoning

Pyridostigmine bromide (PB) is approved for pretreatment against the chemical nerve agent Soman (GD). PB has not been approved for use against other chemical nerve agents including Sarin (GB), Tabun (GA) and VX. Nerve agents work by making your muscles weak. They can make you lose control of your muscles. You can die if your breathing muscles are paralyzed.

Your main protection against chemical weapons is your chemical protective mask and battle dress overgarment. You also have other items to help you ifyou are exposed to chemical warfare agents. These items are:

1. Two antidotes (atropine and 2-PAM)
2. PB is approved as a pretreatment against a soman nerve agent attack. The approval is based on safety studies in humans and effectiveness (how well it works) studies conducted in animals. The FDA has approved PB based only on animal studies of effectiveness because it is not ethical to do these studies in humans. Human studies would require exposing people to the deadly effects of nerve agents, risking poisoning them or even killing them. Studies in monkeys and guinea pigs show that pretreatment with PB makes the antidotes (atropine and 2-PAM) work better against soman (GD). PB pretreatment in animals has not been shown to make the antidotes (atropine and 2-PAM) work better against other nerve agents. Based on the animal studies of whether PB works against soman, it is thought that any potential benefits from use of PB occur only if:

1. PB is taken with enough time before, but not right before, exposure to the nerve agent soman. (If PB is taken right before (when the nerve gas attack alarm is given) or during nerve agent exposure, it may not work and may make the effects of soman worse.)
2. Atropine and 2-PAM are used when symptoms of nerve agent poisoning occur.

How To Take Your PB

1. Your chain of command will tell you when it is time to take PB. This decision will be based on the threat of exposure to soman nerve agent.
2. You must take 1 tablet of PB by mouth every 24 hours with a meal that is medium-fat medium calorie (e.g., 650 calories and 40% fat) or high-fat high calorie (e.g., 1000 calories and 50% fat). Do not take PB on an empty stomach. Take daily until your chain of command tells you to stop taking PB. PB should not be taken with alcohol.
3. Do not take PB more often than you are told. If you miss a dose of PB, take the missed dose as soon as possible, then take the next dose 24 hours after taking the missed dose. This will put you back on schedule. Do not double up on your dose or take extra doses of PB.
4. There is no known advantage to taking extra PB right before soman exposure.
5. Do not continue to take PB after nerve agent exposure has occurred, instead:
6. If you experience most or all of the Mild symptoms of nerve agent poisoning, you should Immediately hold your breath (Do Not Inhale) and Put On Your Protective Mask. Then administer atropine and 2-PAM.
7. Contact your unit medical officer if side effects from PB continue and limit duty performance.

Who should not take PB?

Do not Take PB if you:

- have a history of bowel or bladder blockage (obstruction)
- are allergic to anticholinesterase medicines (certain drugs used during surgery like physostigmine, edrophonium, neostigmine, and ambenonium)

Tell your doctor or medic before taking PB if you:

- are pregnant
- have asthma
- are allergic to bromide
- take blood pressure medicine
- have high eye pressure (glaucoma)
- have problems with your kidneys (renal impairment)

Also, tell your doctor about all your other medical conditions you may have including heart problems, or reflux esophagitis (GERD).

Side Effects

- stomach cramps or pain
- watery eyes
- gas
- blurred vision
- diarrhea
- runny nose
- nausea
- difficulty or tightness in breathing
- frequent urination

- acid stomach (including heartburn or reflux)
- increased salivation
- tingling of fingers, toes, arms, and legs
- sweating
- muscle twitching or weakness
- headaches
- muscle cramps, aches, or pain
- dizziness
- painful menstrual cramps or periods

If your side effects do not go away, see your unit doctor or medic.

This is not a complete list of symptoms that may occur. See your unit doctor right away if your side effects are very bad or for any symptoms that concern you.

About your rights and welfare: DOD may collect information on the use of PB to help decide how best to protect deployed forces in the future. Information that identifies you will remain private (confidential). However, the FDA may review any data collected by DOD for the purpose of evaluating PB. Direct questions about your rights and welfare to your unit medical officer, or e-mail questions to hsrrb@det.amedd.army.mil.

For more information about PB: Talk to your unit medical officer or medic. You can also e-mail questions about PB directly to the U.S. Army Medical Research and Materiel Command at address hsrrb@det.amedd.army.mil.

Manufactured and Distributed by:

Amneal Specialty, a division of Amneal Pharmaceuticals LLC
Bridgewater, NJ 08807 Issued 10/2024